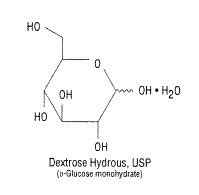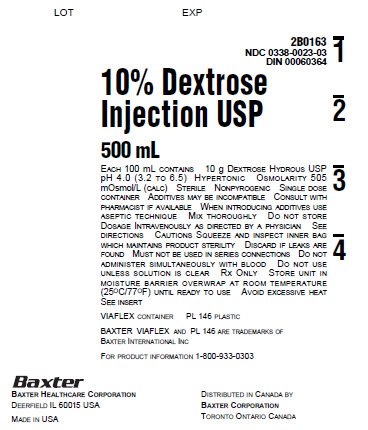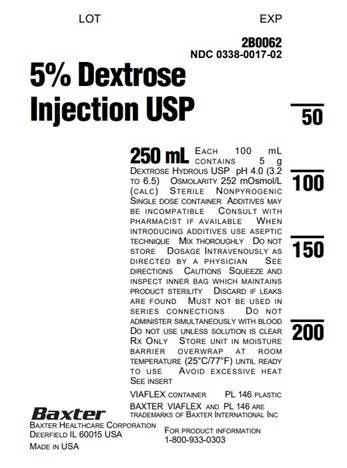 DRUG LABEL: DEXTROSE
NDC: 0338-0017 | Form: INJECTION, SOLUTION
Manufacturer: Baxter Healthcare Corporation
Category: prescription | Type: HUMAN PRESCRIPTION DRUG LABEL
Date: 20241119

ACTIVE INGREDIENTS: DEXTROSE MONOHYDRATE 50 g/1000 mL
INACTIVE INGREDIENTS: WATER

HIGHLIGHTS OF PRESCRIBING INFORMATION

These highlights do not include all the information needed to use DEXTROSE INJECTION safely and effectively. See full prescribing information for DEXTROSE INJECTION.
DEXTROSE injection, for intravenous use
Initial U.S. Approval: 1940

RECENT MAJOR CHANGES

Contraindications (4) 08/2019

Warnings and Precautions (5.1, 5.2, 5.3, 5.4, 5.5, 5.6) 08/2019

1 INDICATIONS AND USAGE

Dextrose Injection is indicated as a source of water and calories. (1)

2 DOSAGE AND ADMINISTRATION

- Only for intravenous infusion. (2.1)
- See full prescribing information for information on preparation, administration, dosing considerations and instructions for use. (2.1, 2.2, 2.3)

3 DOSAGE FORMS AND STRENGTHS

Injection:

- 5% (0.05 grams/mL): 5 grams of dextrose hydrous per 100 mL in single-dose partial-fill flexible containers: 25 mL, 50 mL, 100 mL, 250 mL, 500 mL, and 1000 mL. (3)
- 10% (0.1 grams/mL): 10 grams of dextrose hydrous per 100 mL in partial-fill flexible containers: 250 mL, 500 mL, and 1000 mL. (3)

4 CONTRAINDICATIONS

- Clinically significant hyperglycemia. (4)
- Known hypersensitivity to dextrose. (4)

5 WARNINGS AND PRECAUTIONS

- Hyperglycemia or Hyperosmolar Hyperglycemic State: Monitor blood glucose and administer insulin as needed. (5.1)
- Hypersensitivity Reactions: Monitor for signs and symptoms and discontinue infusion if reactions occur. (5.2)
- Vein Damage and Thrombosis: Consider central vein when administering more than 5% dextrose or with an osmolarity of at least 900 mOsm/L or when there is peripheral vein irritation, phlebitis, and/or associated pain. (2.2, 5.3)
- Hyponatremia: Avoid in patients with or at risk for hyponatremia. If use cannot be avoided, monitor serum sodium concentrations. (5.4)
- Electrolyte Imbalance and Fluid Overload: Avoid in patients with or at risk for fluid and/or solute overloading. If use cannot be avoided, monitor daily fluid balance, electrolyte concentrations, and acid-base balance, as needed and especially during prolonged use. (5.5)
- Refeeding Syndrome: Monitor severely undernourished patients and slowly increase nutrient intake. (5.6)

6 ADVERSE REACTIONS

The most common adverse reactions are, hyperglycemia, hypersensitivity reactions, hyponatremia, infection both systemic and at the injection site, vein thrombosis or phlebitis, and electrolyte imbalance. (6)

To report SUSPECTED ADVERSE REACTIONS, contact Baxter Healthcare at 1-866-888-2472 or FDA at 1-800-FDA-1088 or www.fda.gov/medwatch.

7 DRUG INTERACTIONS

Other Products that Affect Glycemic Control, Vasopressin or Fluid and/or Electrolyte Balance: Monitor blood glucose concentrations, fluid balance, serum electrolyte concentrations and acid-base balance. (7.1)

8 USE IN SPECIFIC POPULATIONS

Pediatric Use: Increased risk of hypoglycemia/hyperglycemia; monitor serum glucose concentrations. (8.4)

FULL PRESCRIBING INFORMATION

1 INDICATIONS AND USAGE

Dextrose Injection is indicated as source of water and calories.

2 DOSAGE AND ADMINISTRATION

2.1 Important Administration Instructions

- Dextrose Injection is intended for intravenous use.
- Peripheral administration of 5% dextrose is generally acceptable, however, consider central vein when administering more than 5% dextrose or with an osmolarity of at least 900 mOsm/L or when there is peripheral vein irritation, phlebitis, and/or associated pain [see Warnings and Precautions (5.3)].
- Do not administer Dextrose Injection simultaneously with blood products through the same administration set because of the possibility of pseudoagglutination or hemolysis.
- To prevent air embolism, use a non-vented infusion set or close the vent on a vented set, avoid multiple connections, do not connect flexible containers in series, fully evacuate residual gas in the container prior to administration, do not pressurize the flexible container to increase flow rates, and if administration is controlled by a pumping device, turn off pump before the container runs dry.
- Prior to infusion, visually inspect the diluted dextrose solution for particulate matter. The solution should be clear and there should be no precipitates. Do not administer unless solution is clear and container is undamaged.
- Use of a final filter is recommended during administration of parenteral solutions, where possible.

2.2 Recommended Dosage

The choice of dextrose concentration, rate and volume depends on the age, weight, clinical and metabolic conditions of the patient and concomitant therapy. Electrolyte supplementation may be indicated according to the clinical needs of the patient.

The administration rate should be governed, especially for premature infants with low birth weight, during the first few days of therapy, by the patient’s tolerance to dextrose.

Increase the infusion rate gradually as indicated by frequent monitoring of blood glucose concentrations [ see Warnings and Precautions (5.1), Use in Specific Populations (8.4)].

2.3 Instructions for Use

To Open

- Do not remove from overpouch until ready to use.
- Tear overwrap down side at slit and remove solution container. Small amounts of moisture may be found on the solution container from water permeating from inside the container. The amount of permeated water is insufficient to affect the solution significantly. If larger amounts of water are found, the container should be checked for tears or leaks.
- Visually inspect the container. Some opacity of the plastic due to moisture absorption during the sterilization process may be observed. This is normal and does not affect the solution quality or safety. The opacity will diminish gradually. Evaluate the following:
  - If the outlet port protector is damaged, detached, or not present, discard container.
  - Check to ensure the solution is clear and there are no precipitates. Discard if there is a color change and/or the appearance of precipitates, insoluble complexes or crystals.
  - Check for minute leaks by squeezing the inner bag firmly. If leaks are found, discard container.

Preparation for Administration

1. Suspend container from eyelet support.
2. Remove protector from outlet port at bottom of container.
3. Attach administration set. Refer to complete directions accompanying set.

To Add Medication

- Additives may be incompatible. Complete information is not available. Do not use additives known or determined to be incompatible.
- Consult with pharmacist, if available. If, in the informed judgment of the healthcare provider, it is deemed advisable to introduce additives, use aseptic technique.
- When introducing additives, consult the instructions for use of the medication to be added and other relevant literature.
- Before adding a substance or medication, verify that it is soluble and/or stable in Dextrose Injection and that the pH range of Dextrose Injection is appropriate.

To Add Medication Before Solution Administration

1. Prepare medication site.
2. Using syringe with 19 to 22 gauge needle, puncture resealable medication port and inject.
3. Mix solution and medication thoroughly. For high density medication such as potassium chloride, squeeze ports while ports are upright and mix thoroughly.
4. After addition, check to ensure the solution is clear and there are no precipitates. Discard if there is a color change and/or the appearance of precipitates, insoluble complexes or crystals.

To Add Medication During Solution Administration

1. Close clamp on the set.
2. Prepare medication site.
3. Using syringe with 19 to 22 gauge needle, puncture resealable medication port and inject.
4. Remove container from IV pole and/or turn to an upright position.
5. Evacuate both ports by squeezing them while container is in the upright position.
6. Mix solution and medication thoroughly.
7. After addition, check to ensure the solution is clear and there are no precipitates. Discard if there is a color change and/or the appearance of precipitates, insoluble complexes or crystals, do not use.
8. Return container to in-use position and continue administration.

Storage

- Use promptly; do not store solutions containing additives.
- Single-dose container.
- Discard any unused portion.

3 DOSAGE FORMS AND STRENGTHS

Dextrose Injection, USP is a clear, sterile, non-pyrogenic solution of dextrose in single-dose containers:

- 5% (0.05 grams/mL): 5 grams of dextrose hydrous per 100 mL in partial-fill flexible containers: 25 mL, 50 mL, 100 mL, 250 mL, 500 mL, and 1000 mL
- 10% (0.1 grams/mL): 10 grams of dextrose hydrous per 100 mL in partial-fill flexible containers: 250 mL, 500 mL, and 1000 mL

4 CONTRAINDICATIONS

The use of Dextrose Injection is contraindicated in patients with:

- Clinically significant hyperglycemia [see Warnings and Precautions (5.1)].
- Known hypersensitivity to dextrose [see Warnings and Precautions (5.2)].

5 WARNINGS AND PRECAUTIONS

5.1 Hyperglycemia and Hyperosmolar Hyperglycemic State

The use of dextrose infusions in patients with impaired glucose tolerance may worsen hyperglycemia. Administration of dextrose at a rate exceeding the patient’s utilization rate may lead to hyperglycemia, coma, and death.

Hyperglycemia is associated with an increase in serum osmolality, resulting in osmotic diuresis, dehydration and electrolyte losses [see Warnings and Precautions (5.5)]. Patients with underlying CNS disease and renal impairment who receive dextrose infusions, may be at greater risk of developing hyperosmolar hyperglycemic state.

Monitor blood glucose levels and treat hyperglycemia to maintain levels within normal limits while administering Dextrose Injection. Insulin may be administered or adjusted to maintain optimal blood glucose levels during Dextrose Injection administration.

5.2 Hypersensitivity Reactions

Hypersensitivity and infusion reactions, including anaphylaxis, have been reported with Dextrose Injection [see Adverse Reactions (6)]. Stop infusion immediately and treat patient accordingly if signs or symptoms of a hypersensitivity reaction develop. Appropriate therapeutic countermeasures must be instituted as clinically indicated.

5.3 Vein Damage and Thrombosis

Peripheral administration of 5% Dextrose Injection is generally acceptable, however, consider central vein when administering more than 5% dextrose or with an osmolarity of ≥ at least 900 mOsm/L or when there is peripheral vein irritation, phlebitis, and/or associated pain [see Dosage and Administration (2. 1)]. The infusion of hypertonic solutions into a peripheral vein may result in vein irritation, vein damage, and/or thrombosis. The primary complication of peripheral access is venous thrombophlebitis, which manifests as pain, erythema, tenderness or a palpable cord. Remove the catheter as soon as possible, if thrombophlebitis develops.

5.4 Hyponatremia

10% Dextrose Injection is a hypertonic solution [see Description, Table 1 (11)]. In the body, however, glucose containing fluids can become extremely physiologically hypotonic due to rapid glucose metabolization. Monitoring of serum sodium is particularly important for hypotonic fluids.

Depending on the tonicity of the solution, the volume and rate of infusion, and depending on a patient’s underlying clinical condition and capability to metabolize glucose, intravenous administration of glucose can cause electrolyte disturbances, most importantly hypo- or hyperosmotic hyponatremia. Monitor serum sodium to minimize the risk of hyponatremia.

The risk for hyponatremia is increased in pediatric patients, elderly patients, postoperative patients, those with psychogenic polydipsia, and in patients treated with medications that increase the risk of hyponatremia (such as diuretics, certain antiepileptic and psychotropic medications). Close clinical monitoring may be warranted.

Acute hyponatremia can lead to acute hyponatremic encephalopathy characterized by headache, nausea, seizures, lethargy and vomiting. Patients with brain edema are at particular risk of severe, irreversible and life-threatening brain injury. Patients at increased risk for developing complications of hyponatremia, such as hyponatremic encephalopathy include pediatric patients; women, in particular, premenopausal women; patients with hypoxemia; and in patients with underlying central nervous system disease [see Use in Specific Populations (8.4, 8.5)].

Avoid Dextrose Injection in patients with or at risk for hyponatremia. If use cannot be avoided, monitor serum sodium concentrations.

Rapid correction of hyponatremia is potentially dangerous with risk of serious neurologic complications. Brain adaptations reducing risk of cerebral edema make the brain vulnerable to injury when chronic hyponatremia is too rapidly corrected, which is known as osmotic demyelination syndrome (ODS). To avoid complications, monitor serum sodium and chloride concentrations, fluid status, acid-base balance, and signs of neurologic complications.

High volume infusion must be used with close monitoring in patients with cardiac or pulmonary failure, and in patients with non-osmotic vasopressin release (including SIADH), due to the risk of hospital-acquired hyponatremia.

5.5 Electrolyte Imbalance and Fluid Overload

Electrolyte deficits, particularly in serum potassium and phosphate, may occur during prolonged use of concentrated dextrose solutions.

Depending on the volume and rate of infusion, the patient’s underlying clinical condition and capability to metabolize dextrose, intravenous administration of Dextrose Injection can cause fluid and/or solute overloading resulting in dilution of serum electrolyte concentrations, (including hypoosmotic hyponatremia), overhydration, congested states or pulmonary edema. The risk of dilutional states is inversely proportional to the electrolyte concentrations in the administered solution. The risk of solute overload causing congested states with peripheral and pulmonary edema is directly proportional to the electrolyte concentrations in the solution.

Avoid Dextrose Injection in patients with or at risk for fluid and/or solute overloading. If use cannot be avoided, monitor fluid balance, blood electrolyte levels, concentration of glucose, acid-base balance, correct fluid and electrolyte imbalances during prolonged parenteral therapy or whenever the condition of the patient or the rate of administration warrants such evaluation and acid-base balance as needed and especially during prolonged use. Additional monitoring is recommended for patients with water and electrolyte disturbances that could be aggravated by increased glucose, insulin administration and/or free water load. Patients at increased risk for developing hyponatremic encephalopathy include pediatric patients; elderly patients, women, in particular premenopausal women; patients with hypoxemia; and patients with underlying CNS disease [see Use in Specific Populations (8.4, 8.5)].

5.6 Refeeding Syndrome

Refeeding severely undernourished patients may result in refeeding syndrome, characterized by the intracellular shift of potassium, phosphorus, and magnesium as the patient becomes anabolic. Thiamine deficiency and fluid retention may also develop. To prevent these complications, monitor severely undernourished patients and slowly increase nutrient intake.

6 ADVERSE REACTIONS

The following adverse reactions associated with the use of dextrose injection were identified in clinical trials or postmarketing reports. Because these reactions were reported voluntarily from a population of uncertain size, it is not always possible to estimate their frequency, reliably, or to establish a causal relationship to drug exposure.

The following clinically significant adverse reactions are described elsewhere in the labeling:

- Hyperglycemia and hyperosmolar hyperglycemic state [see Warnings and Precautions (5.1)]
- Hypersensitivity Reactions: anaphylaxis, pruritis, bronchospasm, cyanosis, angioedema, hypotension, pyrexia, chills, and rash [see Warnings and Precautions (5.2)]
- Infusion Site Reactions: infusion site phlebitis, infusion site erythema, vein damage and thrombosis, and infusion site thrombophlebitis (10% dextrose only) [see Warnings and Precautions (5.3)]
- Hyponatremia and hyponatremic encephalopathy [see Warnings and Precautions (5.4)]
- Electrolyte imbalance, fluid overload andhypervolemia [see Warnings and Precautions (5.5)]
- Refeeding syndrome [see Warnings and Precautions (5.6)]
- Pulmonary vascular precipitates (10% dextrose only)

7 DRUG INTERACTIONS

7.1 Other Products that Affect Glycemic Control, Vasopressin or Fluid and/or Electrolyte Balance

Dextrose Injection can affect glycemic control, vasopressin and fluid and/or electrolyte balance [see Warnings and Precautions (5.1, 5.4, 5.5)]. Monitor blood glucose concentrations, fluid balance, serum electrolyte concentrations and acid-base balance when using Dextrose Injection in patients treated with other substances that affect glycemic control, vasopressin or fluid and/or electrolyte balance.

8 USE IN SPECIFIC POPULATIONS

8.1 Pregnancy

Risk Summary

Appropriate administration of Dextrose Injection during pregnancy is not expected to cause adverse developmental outcomes, including congenital malformations. Animal reproduction studies have not been conducted with injectable dextrose solutions.

The estimated background risk of major birth defects and miscarriage for the indicated population is unknown. All pregnancies have a background risk of birth defect, loss, or other adverse outcomes. In the U.S. general population, the estimated background risk of major birth defects and miscarriage in clinically recognized pregnancies is 2 to 4% and 15 to 20%, respectively.

8.2 Lactation

Risk Summary

There are no data on the presence of dextrose in human milk, the effects on a breastfed infant, or the effects on milk production. The lack of clinical data during lactation precludes a clear determination of the risk of Dextrose Injection to an infant during lactation; therefore, the developmental and health benefits of breastfeeding should be considered along with the mother’s clinical need for Dextrose Injection and any potential adverse effects on the breastfed infant from Dextrose Injection or from the underlying maternal condition.

8.4 Pediatric Use

The safety profile of Dextrose Injection in pediatric patients is similar to adults.

Neonates, especially premature infants with low birth weight, are at increased risk of developing hypo- or hyperglycemia and therefore need close monitoring during treatment with intravenous glucose infusions to ensure adequate glycemic control in order to avoid potential long-term adverse effects.

Closely monitor plasma electrolyte concentrations in pediatric patients who may have impaired ability to regulate fluids and electrolytes. In very low birth weight infants, excessive or rapid administration of Dextrose Injection may result in increased serum osmolality and risk of intracerebral hemorrhage.

Children (including neonates and older children) are at increased risk of developing hyponatremia as well as for developing hyponatremic encephalopathy [see Warnings and Precautions (5.4)].

8.5 Geriatric Use

Clinical studies of Dextrose Injection did not include sufficient numbers of subjects aged 65 and over to determine whether they respond differently from younger subjects. Elderly patients are at increased risk of developing hyponatremia as well as for developing hyponatremic encephalopathy [see Warnings and Precautions (5.4)]. Other reported clinical experience has not identified differences in responses between the elderly and younger patients. In general, dose selection for an elderly patient should be cautious, usually starting at the low end of the dosing range, reflecting the greater frequency of decreased hepatic, renal, or cardiac function, and of concomitant disease or other drug therapy.

Dextrose is known to be substantially excreted by the kidney, and the risk of toxic reactions to this drug may be greater in patients with impaired renal function. Because elderly patients are more likely to have decreased renal function, care should be taken in dose selection, and it may be useful to monitor renal function.

10 OVERDOSAGE

An increased infusion rate of Dextrose Injection or administration of dextrose solutions can cause hyperglycemia, hyperosmolality, and adverse effects on water and electrolyte balance [see Warnings and Precautions (5.1, 5.5)].

Severe hyperglycemia and severe dilutional hyponatremia, and their complications, can be fatal. Discontinue infusion, reduce dose and institute appropriate corrective measures such as administration of exogenous insulin.

Discontinue infusion and institute appropriate corrective measures in the event of overhydration or solute overload during therapy, with particular attention to CNS, respiratory and cardiovascular systems.

If over-exposure occurs, call your Poison Control Center at 1-800-222-1222 for current information on the management of poisoning or overdosage.

11 DESCRIPTION

Dextrose Injection, 5% and 10% USP are sterile, non-pyrogenic solutions of Dextrose, USP in Water for Injection in a polyvinylchloride flexible plastic container for intravenous administration as a source of water and calories.

Partial-fill containers, designed to facilitate admixture when necessary, are available in 25 mL, 50 mL, 100 mL, 250 mL, 500 mL, and 1000 mL sizes. See Table 1 for the content and characteristics of this solution.

The solution contains no bacteriostatic, antimicrobial agent or added buffer and is intended only for use as a single-dose injection. The pH range is 4.0 (3.2 to 6.5).

Water can permeate from inside the container into the overwrap but not in amounts sufficient to affect the solution significantly.

Table 1. Contents and Characteristics of Dextrose Injection 5% and 10%, USP
Strength | Fill Volume | Amount of Dextrose Hydrous per Container | kcal [Caloric value calculated on the basis of 3.4 kcal/g of dextrose, hydrous] per Container | Osmolarity (mOsmol per liter)
Dextrose Injection 5%, USP (0.05 grams/mL) | 25 mL Quad pack | 1.25 grams | 4.25 | 252
Dextrose Injection 5%, USP (0.05 grams/mL) | 50 mL Single pack Quad pack Multi pack | 2.5 grams | 8.5 | 252
Dextrose Injection 5%, USP (0.05 grams/mL) | 100 mL Single pack Quad pack Multi pack | 5 grams | 17 | 252
Dextrose Injection 5%, USP (0.05 grams/mL) | 250 mL | 12.5 grams | 42.5 | 252
Dextrose Injection 5%, USP (0.05 grams/mL) | 500 mL | 25 grams | 85 | 252
Dextrose Injection 5%, USP (0.05 grams/mL) | 1000 mL | 50 grams | 170 | 252
Dextrose Injection 10%, USP (0.1 grams/mL) | 250 mL | 25 grams | 85 | 505
Dextrose Injection 10%, USP (0.1 grams/mL) | 500 mL | 50 grams | 170 | 505
Dextrose Injection 10%, USP (0.1 grams/mL) | 1000 mL | 100 grams | 340 | 505

Dextrose, USP is chemically designated D-glucose, monohydrate (C6H12O6 • H2O), a hexose sugar freely soluble in water. The molecular weight of dextrose (D-glucose) monohydrate is 198.17. It has the following structural formula:

Water for Injection, USP is chemicaly designated H2O.

Dextrose is derived from corn.

The VIAFLEX Plus plastic container is fabricated from a specially formulated polyvinyl chloride (PL 146 Plastic). VIAFLEX Plus on the container indicates the presence of a drug additive in a drug vehicle. The VIAFLEX Plus plastic container system utilizes the same container as the VIAFLEX plastic container system. The amount of water that can permeate from inside the container into the overwrap is insufficient to affect the solution significantly. Solutions in contact with the plastic container can leach out certain of its chemical components in very small amounts within the expiration period, e.g., di-2-ethylhexyl phthalate (DEHP), up to 5 parts per million. However, the safety of the plastic has been confirmed in tests in animals according to USP biological tests for plastic containers as well as by tissue culture toxicity studies.

12 CLINICAL PHARMACOLOGY

12.1 Mechanism of Action

Dextrose is oxidized to carbon dioxide and water, yielding energy.

16 HOW SUPPLIED/STORAGE AND HANDLING

Dextrose Injection 5% and 10%, USP are clear, colorless, sterile solutions of dextrose supplied in a single-dose, partial-fill flexible containers.

Product Description | Size | Code | NDC
Dextrose Injection 5%, USP (0.05 grams/mL) | 25 mL Quad pack | 2B0080 | 0338-0017-10
Dextrose Injection 5%, USP (0.05 grams/mL) | 50 mL Single pack Quad pack Multi pack | 2B0086 2B0081 2B0088 | 0338-0017-41 0338-0017-11 0338-0017-31
Dextrose Injection 5%, USP (0.05 grams/mL) | 100 mL Single pack Quad pack Multi pack | 2B0087 2B0082 2B0089 | 0338-0017-48 0338-0017-18 0338-0017-38
Dextrose Injection 5%, USP (0.05 grams/mL) | 250 mL 500 mL 1000 mL | 2B0062 2B0063 2B0064 | 0338-0017-02 0338-0017-03 0338-0017-04
Dextrose Injection 10%, USP (0.1 grams/mL) | 250 mL 500 mL 1000 mL | 2B0162 2B0163 2B0164 | 0338-0023-02 0338-0023-03 0338-0023-04

Do not remove container from the overwrap until intended for use.

Use the product immediately after mixing and the introduction of additives.

Exposure of pharmaceutical products to heat should be minimized. Avoid excessive heat. It is recommended the product be stored at room temperature (25°C/77°F); brief exposure up to 40°C/104°F does not adversely affect the product.

17 PATIENT COUNSELING INFORMATION

Inform patients, caregivers, or home healthcare providers of the following risks of Dextrose Injection:

- Hyperglycemia and hyperosmolar hyperglycemic state [see Warnings and Precautions (5.1)]
- Hypersensitivity reactions [see Warnings and Precautions (5.2)]
- Vein damage and thrombosis [see Warnings and Precautions (5.3)]
- Hyponatremia [see Warnings and Precautions (5.4)]
- Electrolyte imbalance and fluid overload [see Warnings and Precautions (5.5)]
- Refeeding syndrome [see Warnings and Precautions (5.6)]

Manufactured by, Packed by, Distributed by:

Baxter Healthcare Corporation
Deerfield, IL 60015 USA
Printed in USA

Baxter and Viaflex are trademarks of Baxter International Inc.

PACKAGE/LABEL PRINCIPAL DISPLAY PANEL

Container Label

Container Label

LOT

EXP

2B0063
NDC 0038-0023-03
DIN 00060364

10% Dextrose
Injection USP

500 mL

1

2

3

4

Each 100 mL contain 10 g Dextrose Hydrous USP
pH 4.0 (3.2 to 6.5) Hypertonic Osmolarity 505
mOsmol/L (calc) Sterile Nonpyrogenic Single dose
container Additives may be incompatible Consult with
pharmacist if available When introducing additives use
aseptic technique Mix thoroughly Do not store
Dosage Intravenously as directed by a physician See
directions Cautions Squeeze and inspect inner bag
which maintains product sterility Discard if leaks are
found Must not be used in series connections Do not
administer simultaneously with blood Do not use
unless solution is clear Rx Only Store unit in
moisture barrier overwrap at room temperature
(25°C/77°F) until ready to use Avoid excessive heat
See insert

Viaflex container PL 146 plastic

BAXTER VIAFLEX and PL 146 are trademarks of
Baxter International Inc

For product information 1-800-933-0303

Baxter logo
Baxter Healthcare Corporation
Deerfield, IL 60015 USA
Made in USA

Distribute in Canada By
Baxter Corporation
Toronto Ontario Canada

Container Label

Container Label

LOT

EXP

2B0062
NDC 0038-0017-02

5% Dextrose
Injection USP

50

100

150

200

250 mL

Each 100 mL
contain 5 g
Dextrose Hydrous USP pH 4.0 (3.2 to 6.5)
Osmolarity 252 mOsmol/L (calc)
Sterile Nonpyrogenic
Single dose container Additives may
be incompatible Consult with
pharmacist if available When
introducing additives use aseptic
technique Mix thoroughly Do not
store Dosage Intravenously as
directed by a physician See
directions Cautions Squeeze and
inspect inner bag which maintains
product sterility Discard if leaks
are found Must not be used in
series connections Do not
administer simultaneously with blood
Do not use unless solution is clear
Rx Only Store unit in moisture
barrier overwrap at room
temperature (25°C/77°F) until ready
to use Avoid excessive heat
See insert

Viaflex container PL 146 plastic

BAXTER VIAFLEX and PL 146 are
trademarks of Baxter International Inc

For product information 1-800-933-0303

Baxter logo
Baxter Healthcare Corporation
Deerfield, IL 60015 USA
Made in USA